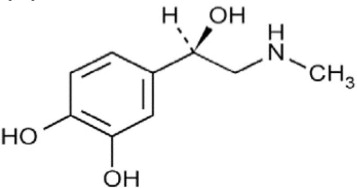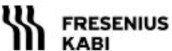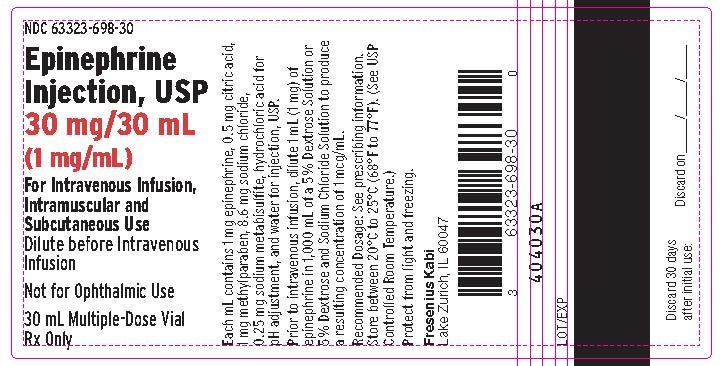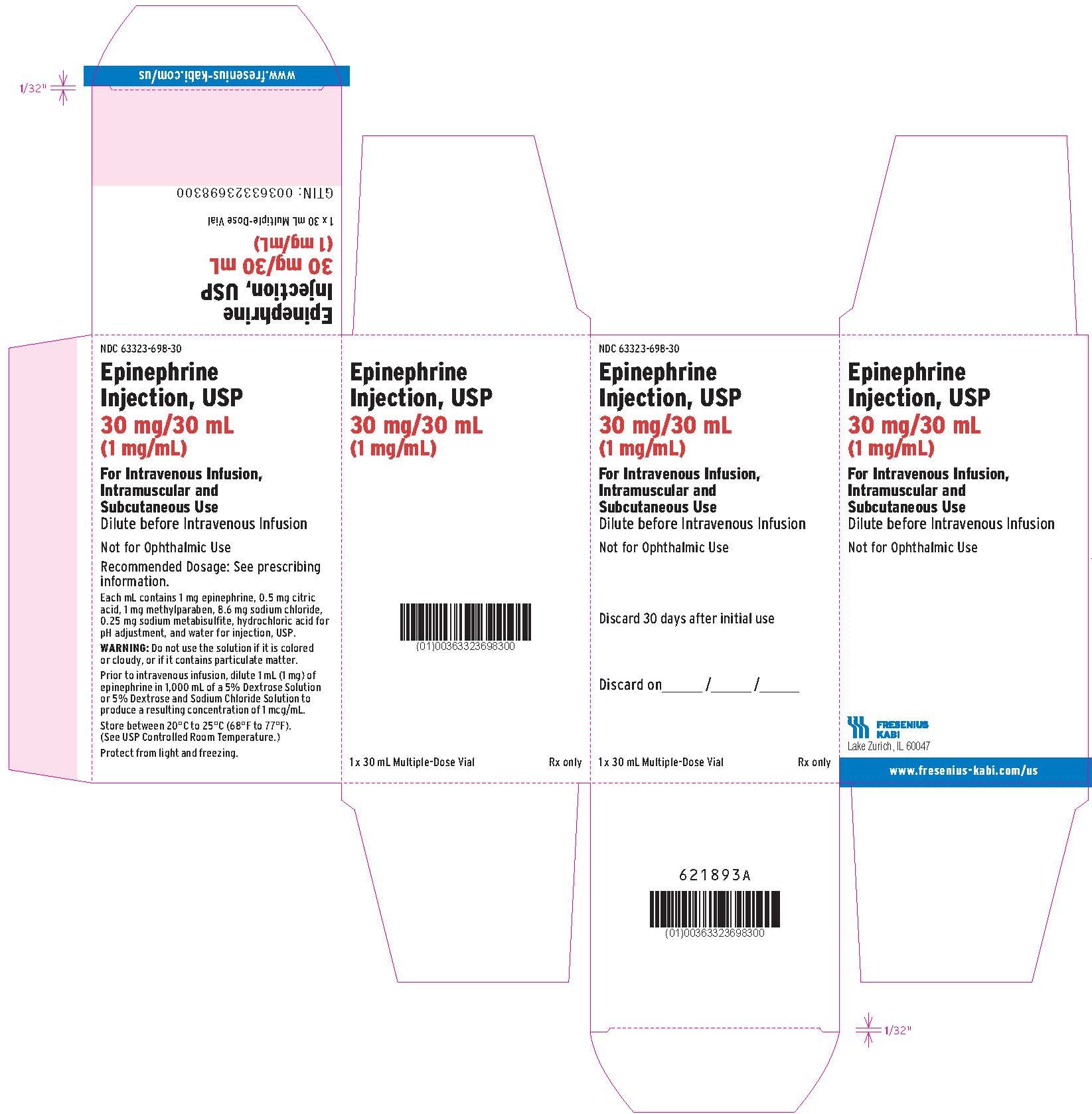 DRUG LABEL: EPINEPHRINE
NDC: 63323-698 | Form: INJECTION, SOLUTION, CONCENTRATE
Manufacturer: Fresenius Kabi USA, LLC
Category: prescription | Type: HUMAN PRESCRIPTION DRUG LABEL
Date: 20250327

ACTIVE INGREDIENTS: EPINEPHRINE 1 mg/1 mL
INACTIVE INGREDIENTS: SODIUM CHLORIDE 8.6 mg/1 mL; HYDROCHLORIC ACID; WATER; SODIUM METABISULFITE; ANHYDROUS CITRIC ACID; METHYLPARABEN

HIGHLIGHTS OF PRESCRIBING INFORMATION

These highlights do not include all the information needed to use EPINEPHRINE INJECTION safely and effectively. See full prescribing information for EPINEPHRINE INJECTION.
EPINEPHRINE injection, for intravenous, intramuscular, subcutaneous use
Initial U.S. Approval: 1939

1 INDICATIONS AND USAGE

Epinephrine is a non-selective alpha and beta adrenergic agonist indicated:

- For emergency treatment of allergic reactions (Type 1), including anaphylaxis, in adults and pediatric patients. (1.1)
- To increase mean arterial blood pressure in adult patients with hypotension associated with septic shock. (1.2)

2 DOSAGE AND ADMINISTRATION

- Anaphylaxis (2.2):
  - Administer intramuscularly or subcutaneously into anterolateral thigh every 5 to10 minutes as needed.
  - Adults and pediatric patients 30 kg or greater: 0.3 mg to 0.5 mg (0.3 mL to 0.5 mL)
  - Pediatric patients under 30 kg: 0.01 mg/kg (0.01 mL/kg)
- Hypotension associated with septic shock (2.3):
  - Dilute epinephrine in dextrose solution prior to infusion.
  - Infuse epinephrine into a large vein.
  - Titrate 0.05 mcg/kg/min to 2 mcg/kg/min to achieve desired blood pressure.
  - Wean gradually.

3 DOSAGE FORMS AND STRENGTHS

Injection solution: 30 mg/30 mL (1 mg/mL) Multiple Dose Vial (3)

4 CONTRAINDICATIONS

None. (4)

5 WARNINGS AND PRECAUTIONS

- Do not inject into buttocks, digits, hands, or feet. (5.1)
- Avoid extravasation into tissues, which can cause local necrosis. (5.3)
- Monitor patient for acute severe hypertension. (5.4)
- Potential for pulmonary edema, which may be fatal. (5.5)
- May constrict renal blood vessels and decrease urine formation. (5.6)
- May induce potentially serious cardiac arrhythmias or aggravate angina
- pectoris, particularly in patients with underlying heart disease. (5.7)
- Presence of sulfite in this product should not deter use. (5.8)

6 ADVERSE REACTIONS

Most common adverse reactions to systemically administered epinephrine are headache; anxiety; apprehensiveness; restlessness; tremor; weakness; dizziness; sweating; palpitations; pallor; peripheral coldness; nausea/vomiting; and/or respiratory difficulties. Arrhythmias, including fatal ventricular fibrillation, rapid rises in blood pressure producing cerebral hemorrhage, and angina have occurred. (6)

To report SUSPECTED ADVERSE REACTIONS, contact Fresenius Kabi USA, LLC at 1-800-551-7176 or FDA at 1-800-FDA-1088 or www.fda.gov/medwatch

7 DRUG INTERACTIONS

- Drugs that counter the pressor effects of epinephrine include alpha blockers, vasodilators such as nitrates, diuretics, antihypertensives, and ergot alkaloids, phenothiazine antipsychotics. (7.1)
- Drugs that potentiate the effects of epinephrine include sympathomimetics, beta blockers, tricyclic antidepressants, MAO inhibitors, COMT inhibitors, clonidine, doxapram, oxytocin. (7.2)
- Drugs that increase the arrhythmogenic potential of epinephrine include beta blockers, cyclopropane and halogenated hydrocarbon anesthetics, quinidine, antihistamines, exogenous thyroid hormones, diuretics, and cardiac glycosides. Observe for development of cardiac arrhythmias. (7.3)
- Potassium-depleting drugs, including corticosteroids, diuretics, and theophylline, potentiate the hypokalemic effects of epinephrine. (7.4)

8 USE IN SPECIFIC POPULATIONS

- Pregnancy: May cause fetal harm. (8.1)
- Elderly patients and pregnant women may be at greater risk of developing adverse reactions when epinephrine is administered parenterally. (8.1, 8.5)

FULL PRESCRIBING INFORMATION

1 INDICATIONS AND USAGE

1.1 Anaphylaxis

Epinephrine Injection is indicated for emergency treatment of type I allergic reactions, including anaphylaxis, in adults and pediatric patients.

1.2 Hypotension associated with Septic Shock

Epinephrine Injection is indicated to increase mean arterial blood pressure in adult patients with hypotension associated with septic shock.

2 DOSAGE AND ADMINISTRATION

2.1 General Considerations

Inspect visually for particulate matter and discoloration prior to administration, solution should be clear and colorless. Do not use if the solution is colored or cloudy, or if it contains particulate matter.

2.2 Recommended Dosage and Administration Instructions for Anaphylaxis

The recommended dosage of Epinephrine Injection is based on weight and is provided in Table 1. Administer undiluted Epinephrine Injection intramuscularly or subcutaneously in the anterolateral aspect of the thigh.

Table 1 Recommended Dosage of Epinephrine Injection in Adult and Pediatric Patients for Anaphylaxis
 | Dosage | Maximum Dosage
Adult and Pediatric Patients Weighing 30 kg or Greater | 0.3 mg to 0.5 mg (0.3 mL to 0.5 mL) of undiluted Epinephrine Injection | 0.5 mg (0.5 mL) per injection
Pediatric Patients Weighing Less Than 30 kg | 0.01 mg/kg (0.01 mL/kg) of undiluted Epinephrine Injection | 0.3 mg (0.3 mL) per injection

- In the absence of clinical improvement or if symptoms worsen after the initial treatment, additional doses of Epinephrine Injection may be repeated every 5 to 10 minutes as necessary.
- Monitor clinically for cardiac effects.

Administration Instructions

- For intramuscular administration, use a needle long enough (at least 1/2 inch to 5/8 inch) to ensure the injection is administered into the muscle.
- To minimize the risk of injection related injury to a pediatric patient, hold the leg firmly in place and limit movement prior to and during an injection.
- Inject Epinephrine Injection intramuscularly or subcutaneously into the anterolateral aspect of the thigh, through clothing if necessary. Do not inject intravenously, and do not inject into buttocks, into digits, hands or feet.
- Do not administer repeated injections at the same site, as the resulting vasoconstriction may cause tissue necrosis.

2.3 Recommended Dosage and Administration Instructions for Hypotension associated with Septic Shock

Dilute 1 mL (1 mg) of epinephrine from its vial into 1,000 mL of one of the following solutions: 5% Dextrose Injection; 5% Dextrose and 0.9% Sodium Chloride Injection; 5% Dextrose and 0.45% Sodium Chloride Injection; or 5% Dextrose and 0.2% Sodium Chloride Injection. Each mL of this dilution contains 1 mcg of epinephrine. The diluted solutions can be stored for up to 4 hours at room temperature (20°C to 25°C) or 24 hours under refrigerated conditions (2°C to 8°C). Administration in Sodium Chloride Injection alone is not recommended. If indicated, administer whole blood or plasma separately.

Whenever possible, give infusions of epinephrine into a large vein. Avoid using a catheter tie-in technique, because the obstruction to blood flow around the tubing may cause stasis and increased local concentration of the drug. Avoid the veins of the leg in elderly patients or in those suffering from occlusive vascular disorders.

To provide hemodynamic support in septic shock associated hypotension in adult patients, the suggested dosing infusion rate of intravenously administered epinephrine is 0.05 mcg/kg/min to 2 mcg/kg/min, and is titrated to achieve a desired mean arterial pressure (MAP). The dosage may be adjusted periodically, such as every 10 to15 minutes, in increments of 0.05 mcg/kg/min to 0.2 mcg/kg/min, to achieve the desired blood pressure goal. The ideal body weight (IBW) should be used as the weight parameter for dosing epinephrine in adult patients with septic shock associated hypotension.

After hemodynamic stabilization, wean incrementally over time, such as by decreasing doses of epinephrine every 30 minutes over a 12 to 24 hour period.

3 DOSAGE FORMS AND STRENGTHS

Injection: Epinephrine injection USP is a sterile, nonpyrogenic, clear and colorless solution supplied as 30 mg/30 mL(1 mg/mL) in a multiple dose amber glass vial.

4 CONTRAINDICATIONS

None.

5 WARNINGS AND PRECAUTIONS

5.1 Injection-Related Complications for Anaphylaxis

Injection into the anterolateral aspect of the thigh (vastus lateralis muscle) is the most appropriate location for administration because of its location, size, and available blood flow. Injection into (or near) smaller muscles, such as in the deltoid, is not recommended.

Do not administer repeated injections of epinephrine at the same site, as the resulting vasoconstriction may cause tissue necrosis.

Do Not Inject Intravenously

Large doses or accidental intravenous injection of undiluted epinephrine may result in cerebral hemorrhage due to sharp rise in blood pressure. Rapidly acting vasodilators can counteract the marked pressor effects of epinephrine if there is such inadvertent administration.

Do not inject into buttock. Injection into the buttock may not provide effective treatment of anaphylaxis and has been associated with the development of Clostridial infections (gas gangrene).

Do not inject into digits, hands, or feet. Epinephrine is a strong vasoconstrictor. Accidental injection into the digits, hands or feet may result in loss of blood flow to the affected area and tissue necrosis.

5.2 Serious Infections at the Injection Site

Rare cases of serious skin and soft tissue infections, including necrotizing fasciitis and myonecrosis caused by Clostridia (gas gangrene), have been reported at the injection site following epinephrine injection for anaphylaxis. Advise patients to seek medical care if they develop signs or symptoms of infection, such as persistent redness, warmth, swelling, or tenderness, at the epinephrine injection site.

5.3 Extravasation and Tissue Necrosis with Intravenous Infusion

Avoid extravasation of epinephrine into the tissues, to prevent local necrosis. When Epinephrine Injection is administered intravenously, the infusion site should be checked frequently for free flow. Blanching along the course of the infused vein, sometimes without obvious extravasation, may be attributed to vasa vasorum constriction with increased permeability of the vein wall, permitting some leakage. This also may progress on rare occasions to superficial slough. Hence, if blanching occurs, consider changing the infusion site at intervals to allow the effects of local vasoconstriction to subside.

There is a potential for gangrene in a lower extremity when infusions of catecholamine are given in an ankle vein.

Antidote for Extravasation Ischemia: To prevent sloughing and necrosis in areas in which extravasation has taken place, infiltrate the area with 10 mL to 15 mL of saline solution containing from 5 mg to 10 mg of phentolamine, an adrenergic blocking agent. Use a syringe with a fine hypodermic needle, with the solution being infiltrated liberally throughout the area, which is easily identified by its cold, hard, and pallid appearance. Sympathetic blockade with phentolamine causes immediate and conspicuous local hyperemic changes if the area is infiltrated within 12 hours.

5.4 Hypertension

Because individual response to epinephrine may vary significantly, monitor blood pressure frequently and titrate to avoid excessive increases in blood pressure.

Patients receiving monoamine oxidase inhibitors (MAOI) or antidepressants of the triptyline or imipramine types may experience severe, prolonged hypertension when given epinephrine.

5.5 Pulmonary Edema

Epinephrine increases cardiac output and causes peripheral vasoconstriction, which may result in pulmonary edema.

5.6 Renal Impairment

Epinephrine constricts renal blood vessels, which may result in oliguria or renal impairment.

5.7 Cardiac Arrhythmias and Ischemia

Epinephrine may induce cardiac arrhythmias and myocardial ischemia in patients, especially patients suffering from coronary artery disease, or cardiomyopathy.

5.8 Allergic Reactions Associated with Sulfite

Epinephrine is the preferred treatment for serious allergic or other emergency situations even though this product contains sodium metabisulfite, a sulfite that may in other products cause allergic-type reactions including anaphylactic symptoms or life-threatening or less severe asthmatic episodes in certain susceptible persons. The alternatives to using epinephrine in a life threatening situation may not be satisfactory. The presence of sulfite(s) in this product should not deter administration of the drug for treatment of serious allergic or other emergency situations.

6 ADVERSE REACTIONS

The following adverse reactions associated with the use of epinephrine were identified in clinical use, observational trials, case reports, or postmarketing reports. Because some of these reactions were reported voluntarily from a population of uncertain size, it is not always possible to reliably estimate their frequency or establish a causal relationship to drug exposure.

Adverse reactions are listed below by body system:

Cardiovascular: angina, arrhythmias, cerebral hemorrhage (particularly in elderly patients with cardiovascular disease), hypertension, pallor, palpitations, tachyarrhythmia, tachycardia, vasoconstriction, ventricular ectopy and stress cardiomyopathy.

Gastrointestinal: nausea, vomiting

Metabolism and Nutrition Disorders: transient hyperglycemia, sweating

Neurological: disorientation, dizziness, headache, impaired memory, panic, psychomotor agitation (particularly in patients with Parkinson's disease), sleepiness, tingling, tremor, weakness.

Psychiatric: anxiety, apprehensiveness, restlessness.

Respiratory: respiratory difficulties

Skin and subcutaneous tissue disorders: skin and soft tissue infections, necrotizing fasciitis, myonecrosis (gas gangrene)

7 DRUG INTERACTIONS

7.1 Drugs Antagonizing Pressor Effects of Epinephrine

- α-blockers, such as phentolamine
- Vasodilators, such as nitrates
- Diuretics
- Antihypertensives
- Ergot alkaloids
- Phenothiazine antipsychotics

7.2 Drugs Potentiating Pressor Effects of Epinephrine

- Sympathomimetics
- β-blockers, such as propranolol
- Tricyclic anti-depressants
- Monoamine oxidase (MAO) inhibitors
- Catechol-O-methyl transferase (COMT) inhibitors, such as entacapone
- Clonidine
- Doxapram
- Oxytocin

7.3 Drugs Potentiating Arrhythmogenic Effects of Epinephrine

Cardiac arrhythmias are more common among patients receiving any of the following drugs [see Warnings and Precautions (5.7) and Adverse Reactions (6)]

- β-blockers, such as propranolol
- Cyclopropane or halogenated hydrocarbon anesthetics, such as halothane
- Antihistamines
- Thyroid hormones
- Diuretics
- Cardiac glycosides, such as digitalis glycosides
- Quinidine

7.4 Drugs Potentiating Hypokalemic Effects of Epinephrine

- Potassium depleting diuretics
- Corticosteroids
- Theophylline

8 USE IN SPECIFIC POPULATIONS

8.1 Pregnancy

Risk Summary

Prolonged experience with epinephrine use in pregnant women over several decades, based on published literature, does not identify a drug-associated risk of major birth defects, miscarriage, or adverse maternal or fetal outcomes. There are risks to the mother and fetus associated with anaphylaxis and hypotension associated with shock, and treatment with epinephrine should not be delayed (see Clinical Considerations). In animal reproduction studies, epinephrine administered by the subcutaneous route to pregnant rabbits, mice, and hamsters, during the period of organogenesis, resulted in adverse developmental effects (including gastroschisis, embryonic lethality, and delayed skeletal ossification) at doses approximately 2 times the maximum recommended daily intramuscular, subcutaneous, or intravenous dose (see Data).

The estimated background risk of major birth defects and miscarriage for the indicated population is unknown. All pregnancies have a background risk of birth defect, loss, or other adverse outcomes. In the United States general population, the estimated background risk of major birth defects and miscarriage in clinically recognized pregnancies is 2 to 4% and 15 to 20%, respectively.

Clinical Considerations

Disease-associated maternal and/or embryo/fetal risk

During pregnancy, anaphylaxis can be catastrophic and can lead to hypoxic-ischemic encephalopathy and permanent central nervous system damage or death in the mother and, more commonly, in the fetus or neonate. Treatment of anaphylaxis during pregnancy should not be delayed.

Hypotension associated with septic shock is a medical emergency in pregnancy which can be fatal if left untreated. Delaying treatment in pregnant women with hypotension associated with septic shock may increase the risk of maternal and fetal morbidity and mortality. Life-sustaining therapy for the pregnant woman should not be withheld due to potential concerns regarding the effects of epinephrine on the fetus.

Labor or Delivery

Epinephrine is the first line-medication of choice for treatment of anaphylaxis; it should be used in the same manner for patients in labor or delivery.

Hypotension Associated with Septic Shock

Epinephrine usually inhibits spontaneous or oxytocin induced contractions of the pregnant human uterus and may delay the second stage of labor. Avoid epinephrine during the second stage of labor. In dosage sufficient to reduce uterine contractions, the drug may cause a prolonged period of uterine atony with hemorrhage. Avoid epinephrine in obstetrics when maternal blood pressure exceeds 130/80 mmHg.

Although epinephrine may improve maternal hypotension associated with septic shock, it may result in uterine vasoconstriction, decreased uterine blood flow, and fetal anoxia.

Data

Animal Data

In an embryofetal development study with pregnant rabbits dosed during the period of organogenesis (on days 3 to 5, 6 to 7, or 7 to 9 of gestation), epinephrine caused teratogenic effects (including gastroschisis) at doses approximately 15 times the maximum recommended intramuscular, subcutaneous, or intravenous dose (on a mg/m^2 basis at a maternal subcutaneous dose of 1.2 mg/kg/day for 2 to 3 days). Animals treated on days 6 to 7 had decreased number of implantations.

In an embryofetal development study, pregnant mice were administered epinephrine (0.1 to 10 mg/kg/day) on Gestation Days 6 to 15. Teratogenic effects, embryonic lethality, and delays in skeletal ossification were observed at approximately 3 times the maximum recommended intramuscular, subcutaneous, or intravenous dose (on a mg/m^2 basis at maternal subcutaneous dose of 1 mg/kg/day for 10 days). These effects were not seen in mice at approximately 2 times the maximum recommended daily intramuscular or subcutaneous dose (on a mg/m^2 basis at a subcutaneous maternal dose of 0.5 mg/kg/day for 10 days).

In an embryofetal development study with pregnant hamsters dosed during the period of organogenesis from gestation days 7 to 10, epinephrine produced reductions in litter size and delayed skeletal ossification at doses approximately 2 times the maximum recommended intramuscular, subcutaneous, or intravenous dose (on a mg/m^2 basis at a maternal subcutaneous dose of 0.5 mg/kg/day).

8.2 Lactation

Risk Summary

There is no information regarding the presence of epinephrine in human milk or the effects of epinephrine on the breastfed infant or on milk production. However, due to its poor oral bioavailability and short half-life, epinephrine exposure is expected to be very low in the breastfed infant.

Treatment for anaphylaxis or hypotension associated with septic shock in breastfeeding patients should not be delayed.

8.4 Pediatric Use

Anaphylaxis

The safety and effectiveness of Epinephrine Injection for the emergency treatment of type I allergic reactions, including anaphylaxis, have been established in pediatric patients. The use of Epinephrine Injection for this indication is supported by clinical use data, which support weight-based dosing for treatment of anaphylaxis in pediatric patients, and other reported clinical experience with the use of epinephrine suggests that the adverse reactions seen in pediatric patients are similar in nature and extent to those both expected and reported in adults.

Hypotension Associated with Septic Shock

Safety and effectiveness of epinephrine in pediatric patients with septic shock have not been established.

8.5 Geriatric Use

Anaphylaxis

Clinical studies for the emergency treatment of type I allergic reactions, including anaphylaxis have not been performed in subjects aged 65 and over to determine whether they respond differently from younger subjects. However, other reported clinical experience with use of epinephrine for the emergency treatment of type I allergic reactions, including anaphylaxis, has identified that geriatric patients may be particularly sensitive to the effects of epinephrine. Therefore, for the emergency treatment of type I allergic reactions, including anaphylaxis, consider monitoring geriatric patients for adverse reactions to take into account potential concomitant disease or other drug therapy.

Hypotension Associated with Septic Shock

Clinical studies of epinephrine for the treatment of hypotension associated with septic shock did not include sufficient numbers of subjects aged 65 and over to determine whether they respond differently from younger subjects. Other reported clinical experience has not identified differences in responses between the elderly and younger patients. In general, due to the greater frequency of decreased hepatic, renal, or cardiac function, and of concomitant disease or other drug therapy, consider monitoring geriatric patients for adverse reactions. Avoid the veins in the leg in geriatric patients.

10 OVERDOSAGE

Overdosage of epinephrine may produce extremely elevated arterial pressure, which may result in cerebrovascular hemorrhage, particularly in elderly patients. Overdosage may also result in pulmonary edema because of peripheral vascular constriction together with cardiac stimulation. Epinephrine overdosage may also cause transient bradycardia followed by tachycardia and these may be accompanied by potentially fatal cardiac arrhythmias. Premature ventricular contractions may appear within one minute after injection and may be followed by multifocal ventricular tachycardia (prefibrillation rhythm). Subsidence of the ventricular effects may be followed by atrial tachycardia and occasionally by atrioventricular block. Myocardial ischemia and infarction, cardiomyopathy, extreme pallor and coldness of the skin, metabolic acidosis due to elevated blood lactic acid levels, and renal insufficiency and failure have also been reported.

Epinephrine is rapidly inactivated in the body and treatment following overdose with epinephrine is primarily supportive. Treatment of pulmonary edema consists of a rapidly acting alpha-adrenergic blocking drug (such as phentolamine mesylate) and respiratory support. Treatment of epinephrine associated arrhythmias consists of administration of a beta-adrenergic blocking drug (such as propranolol). If necessary, pressor effects may be counteracted by rapidly acting vasodilators or alpha-adrenergic blocking drugs. If prolonged hypotension follows such measures, it may be necessary to administer another pressor drug.

11 DESCRIPTION

Epinephrine Injection, USP is a clear, colorless, sterile solution containing 1 mg/mL epinephrine, packaged as a 30 mL solution in a multiple dose amber vial. In the 30 mL vial, each 1 mL of Epinephrine Injection, USP solution contains 1 mg epinephrine, 0.5 mg citric acid, 1 mg methylparaben (preservative), 8.6 mg sodium chloride, 0.25 mg sodium metabisulfite, hydrochloric acid for pH adjustment and water for injection. The pH range is 2.2-5.0.

Solution must be diluted prior to intravenous use.

Epinephrine is a sympathomimetic catecholamine. The chemical name of epinephrine is: 1,2-Benzenediol, 4-[(1R)-1-hydroxy-2-(methylamino)ethyl]-, or (-)-3,4-Dihydroxy-α-[2-(methylamino)ethyl]benzyl alcohol. The chemical structure of epinephrine is:

The molecular weight of epinephrine is 183.2.

Epinephrine solution deteriorates rapidly on exposure to air or light, turning pink from oxidation to adrenochrome and brown from the formation of melanin.

12 CLINICAL PHARMACOLOGY

12.1 Mechanism of Action

Anaphylaxis

Epinephrine acts on both alpha- and beta-adrenergic receptors.

Through its action on alpha-adrenergic receptors, epinephrine lessens the vasodilation and increased vascular permeability that occurs during anaphylaxis, which can lead to loss of intravascular fluid volume and hypotension.

Through its action on beta-adrenergic receptors, epinephrine causes bronchial smooth muscle relaxation and helps alleviate bronchospasm, wheezing and dyspnea that may occur during anaphylaxis.

Epinephrine also alleviates pruritus, urticaria, and angioedema. It may also relieve gastrointestinal and genitourinary symptoms associated with anaphylaxis because of its relaxer effects on the smooth muscle of the stomach, intestine, uterus and urinary bladder.

Hypotension

Epinephrine acts on both alpha and beta-adrenergic receptors. The mechanism of the rise in blood pressure is 3-fold: a direct myocardial stimulation that increases the strength of ventricular contraction (positive inotropic action), an increased heart rate (positive chronotropic action), and peripheral vasoconstriction.

12.2 Pharmacodynamics

Epinephrine increases glycogenolysis, reduces glucose up take by tissues, and inhibits insulin release in the pancreas, resulting in hyperglycemia and increased blood lactic acid.

Intravenous use for hypotension associated with septic shock

When administered parenterally, epinephrine has a rapid onset and short duration of action.

Following intravenous administration of epinephrine, increases in systolic blood pressure and heart rate are observed. Decreases in systemic vascular resistance and diastolic blood pressure are observed at low doses of epinephrine because of β2-mediated vasodilation, but are overtaken by α1-mediated peripheral vasoconstriction at higher doses leading to increase in diastolic blood pressure. The onset of blood pressure increase following an intravenous dose of epinephrine is < 5 minutes and the time to offset blood pressure response occurs within 20 min. Most vascular beds are constricted including renal, splanchnic, mucosal and skin.

Epinephrine causes mydriasis when administered parenterally.

12.3 Pharmacokinetics

Following intravenous injection, epinephrine is rapidly cleared from the plasma with an effective half-life of < 5 min. A pharmacokinetic steady state following continuous intravenous infusion is achieved within 10-15 min. In patients with septic shock, epinephrine displays dose-proportional pharmacokinetics in the infusion dose range of 0.03 to 1.7 mcg/kg/min.

Epinephrine is extensively metabolized with only a small amount excreted unchanged.

Epinephrine is rapidly degraded to vanillylmandelic acid, an inactive metabolite, by monoamine oxidase and catechol-O-methyltransferase that are abundantly expressed in the liver, kidneys and other extraneuronal tissues. The tissues with the highest contribution to removal of circulating exogenous epinephrine are the liver (32%), kidneys (25%), skeletal muscle (20%), and mesenteric organs (12%).

Specific Populations

Age

In a pharmacokinetic study of 45-minute epinephrine infusions given to healthy men aged 20 to 25 years and healthy men aged 60 to 65 years, the mean plasma metabolic clearance rate of epinephrine at steady state was greater among the older men (144.8 versus 78 mL/kg/min for a 0.0143 mcg/kg/min infusion).

Body Weight

Body weight has been found to influence epinephrine pharmacokinetics. Higher body weight was associated with a higher plasma epinephrine clearance and a lower concentration plateau.

13 NONCLINICAL TOXICOLOGY

13.1 Carcinogenesis, Mutagenesis, Impairment of Fertility

Long-term studies to evaluate the carcinogenic potential of epinephrine have not been conducted.

Epinephrine and other catecholamines have been shown to have mutagenic potential in vitro. Epinephrine was positive in the Salmonella bacterial reverse mutation assay, positive in the mouse lymphoma assay, and negative in the in vivo micronucleus assay. Epinephrine is an oxidative mutagen based on the E. coli WP2 Mutoxitest bacterial reverse mutation assay. This should not prevent the use of epinephrine under the conditions noted under the Indications and Usage.

The potential for epinephrine to impair reproductive performance has not been evaluated, but epinephrine has been shown to decrease implantation in female rabbits dosed subcutaneously with 1.2 mg/kg/day (15-fold the highest human intramuscular or subcutaneous daily dose) during gestation days 3 to 9.

13.2 Animal Toxicology and/or Pharmacology

Epinephrine was associated with metabolic effects, decreased mesentery, coronary and renal conductance in a sheep model of septic shock. Data from hemolysis study have shown that epinephrine at 1:1000 dilution is non-hemolytic. Epinephrine infusion significantly increased the MAP (69 vs. 86 mmHg) and cardiac output (6.4 vs. 7.1 L/min) and decreased renal blood flow (330 vs. 247 mL/min).

16 HOW SUPPLIED/STORAGE AND HANDLING

Epinephrine Injection is supplied as a clear, colorless solution as follows:

Each carton contains 1 multiple dose vial containing 30 mg/30 mL (1 mg/mL) epinephrine injection, USP in an amber glass vial

NDC 63323-698-30 30 mL Multiple Dose Vial

Epinephrine is light sensitive. Protect from light until ready to use.

Do not refrigerate. Protect from freezing.

Vial and contents must be discarded 30 days after initial use.

Store at room temperature, between 20°C to 25°C (68°F to 77°F). (See USP Controlled Room Temperature.) Protect from alkalis and oxidizing agents.

The container closure is not made with natural rubber latex.

17 PATIENT COUNSELING INFORMATION

Risk of Recurrent Symptoms of Anaphylaxis

Warn patients with a good response to initial treatment about the possibility of recurrence of symptoms and instruct patients to obtain proper medical attention if symptoms return.

Transient Hyperglycemia

Advise patients with diabetes that they may develop increased blood glucose levels following epinephrine administration [see Adverse Reactions (6) and Clinical Pharmacology (12.2)].

Serious Infection at Injection Site

Rare cases of serious skin and soft tissue infections, including necrotizing fasciitis and myonecrosis caused by Clostridia (gas gangrene), have been reported at the injection site following epinephrine injection for anaphylaxis. Advise patients to seek medical care if they develop signs or symptoms of infection, such as persistent redness, warmth, swelling, or tenderness, at the epinephrine injection site [see Warnings and Precautions (5.2)].

Lake Zurich, IL, 60047

For Product Inquiry:
1-800-551-7176 or
www.fresenius-kabi.com/us

451809A

PACKAGE LABEL - PRINCIPAL DISPLAY – Epinephrine Injection, USP 30 mg/ 30 mL Vial

Label

NDC 63323-698-30

Epinephrine

Injection, USP

30 mg/30 mL

(1 mg/mL)

For Intravenous Infusion,

Intramuscular and

Subcutaneous Use

Dilute before Intravenous

Infusion

Not for Ophthalmic Use

30 mL Multiple-Dose Vial

Rx Only

PACKAGE LABEL - PRINCIPAL DISPLAY – Epinephrine Injection, USP 30 mg/ 30 mL

Carton Label

NDC 63323-698-30

Epinephrine

Injection, USP

30 mg/30 mL

(1 mg/mL)

For Intravenous Infusion,

Intramuscular and

Subcutaneous Use

Dilute before Intravenous Infusion

Not for Ophthalmic Use

Discard 30 days after initial use

Discard on ‑‑‑_____/_____/_____

1 x 30 mL Multiple-Dose Vial Rx only